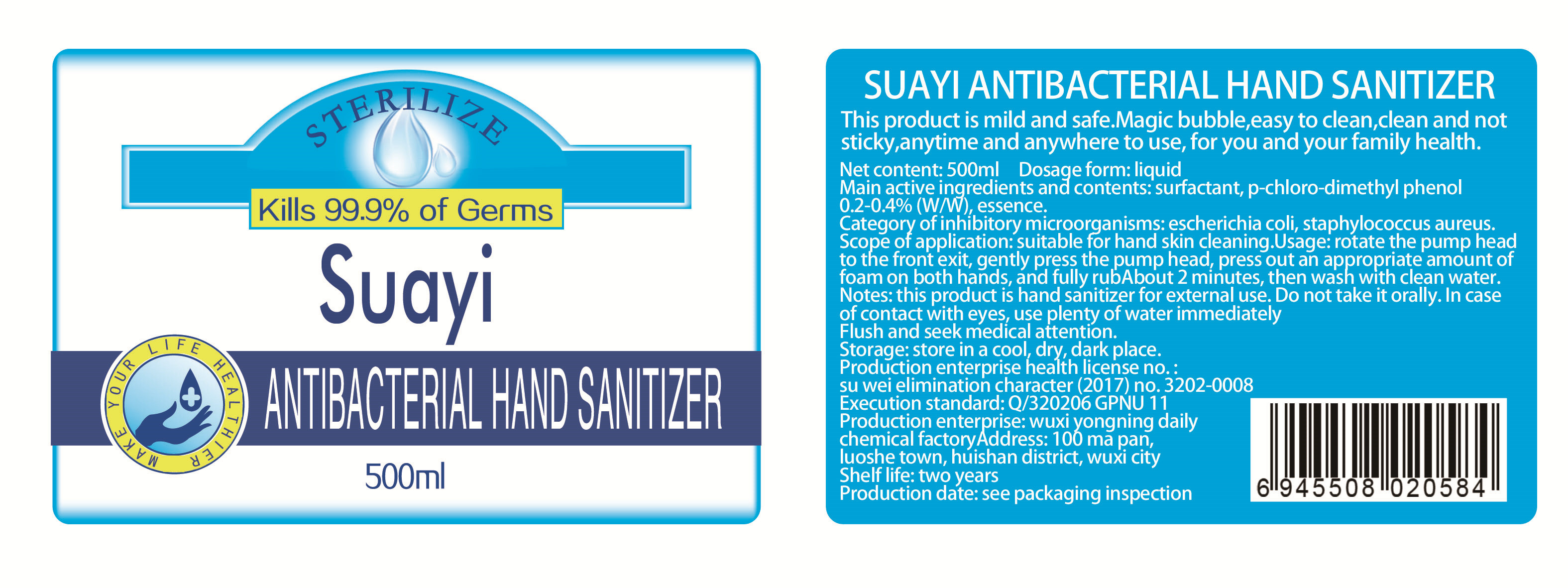 DRUG LABEL: antibacterial hand sanitizer
NDC: 54607-003 | Form: LIQUID
Manufacturer: Wuxi Yongning Daily Chemical Factory
Category: otc | Type: HUMAN OTC DRUG LABEL
Date: 20200329

ACTIVE INGREDIENTS: 2-CHLORO-4,5-DIMETHYLPHENOL 1.5 mg/500 mL
INACTIVE INGREDIENTS: SODIUM LAURETH-5 SULFATE; GLYCERIN; COCAMIDOPROPYL BETAINE; COCAMINE; WATER; METHYLCHLOROISOTHIAZOLINONE; SODIUM CHLORIDE; PROPYLENE GLYCOL; METHYLISOTHIAZOLINONE; EDETIC ACID; MAGNESIUM CHLORIDE

ACTIVE INGREDIENT

P-chloro-m-dimethylphenol

DOSAGE AND ADMINISTRATION

store in a cool, dry, dark place.

keep out of reach of children.

WARNINGS

This product is hand sanitizer for external use.

Do not take it orally. In case of contact with eyes, use plenty of water immediately.

INDICATIONS AND USAGE

Rotate the pump head to the front exit, gently press the pump head, press out an appropriate amount of foam on both hands, and fully rub about 2 minutes, then wash with clean water.

PURPOSE

Disinfection
Sterilization
No Rinseing

INACTIVE INGREDIENT

GLYCERIN
COCAMDOPROPYL BETAINE
COCAMINE
MAGNESIUM CHLORIDE
METMCHL OITHIAOINONE
SODIUM CHLORIDE
PROPYLENE GLYCOL
METHYUSOTHIAZOLINONE
EDETIC ACID
SODIUM LAURETH-5 SULFFATE
WATER